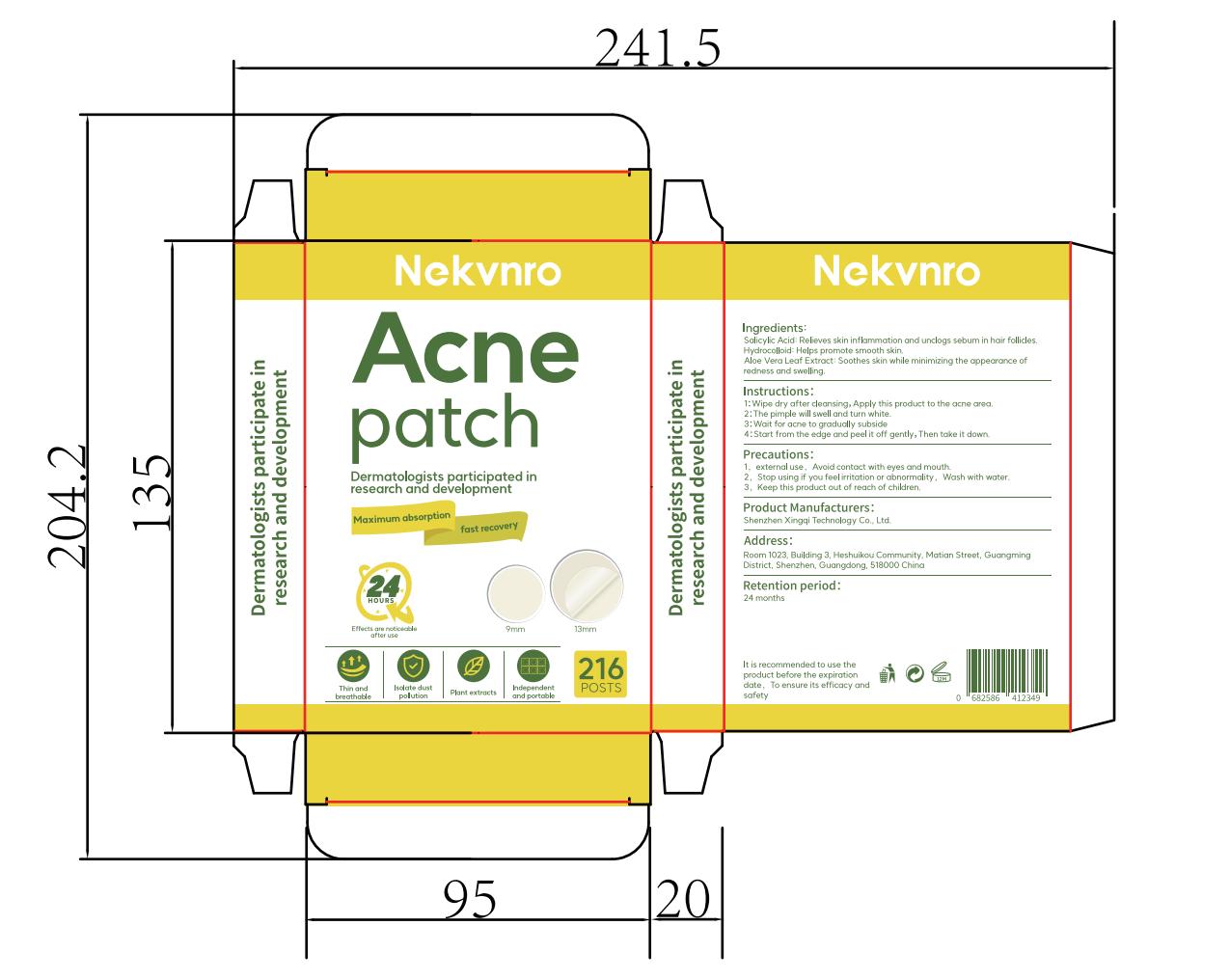 DRUG LABEL: Nekvnro Acne patch
NDC: 84613-051 | Form: PATCH
Manufacturer: Shenzhen Xingqi Technology Co., Ltd.
Category: otc | Type: HUMAN OTC DRUG LABEL
Date: 20240808

ACTIVE INGREDIENTS: SALICYLIC ACID 1 g/100 g; ALOE VERA LEAF 1 g/100 g
INACTIVE INGREDIENTS: SODIUM ALGINATE

ACTIVE INGREDIENT

Salicylic Acid 1%

Aloe Vera Leaf Extract 1%

Purpose

Acne patch

Uses

1: Wipe dry after cleansing, Apply this product to the acne area.
2: The pimple will swell and turn white.
3: Wait for acne to gradually subside
4: Start from the edge and peel it off gently, Then take it down.

Warnings

1，external use,Avoid contact with eyes and mouth.
2，Stop using if you feel irritation or abnormality,Wash with water.
3，Keep this product out of reach of children.

Dosage and administration

For external use only.

Do not use

1,external use，Avoid contact with eyes and mouth.
2,Stop using if you feel irritation or abnormality,Wash with water.
3,Keep this product out of reach of children.

When using section

1，external use，Avoid contact with eyes and mouth.
2，Stop using if you feel irritation or abnormality，Wash with water.
3，Keep this product out of reach of children.

stop use

1，external use，Avoid contact with eyes and mouth.
2，Stop using if you feel irritation or abnormality，Wash with water.
3，Keep this product out of reach of children.

KEEP OUT OF REACH OF CHILDREN SECTION

Keep this product out of reach of children.

Inactive ingredients

Hydrocolloid